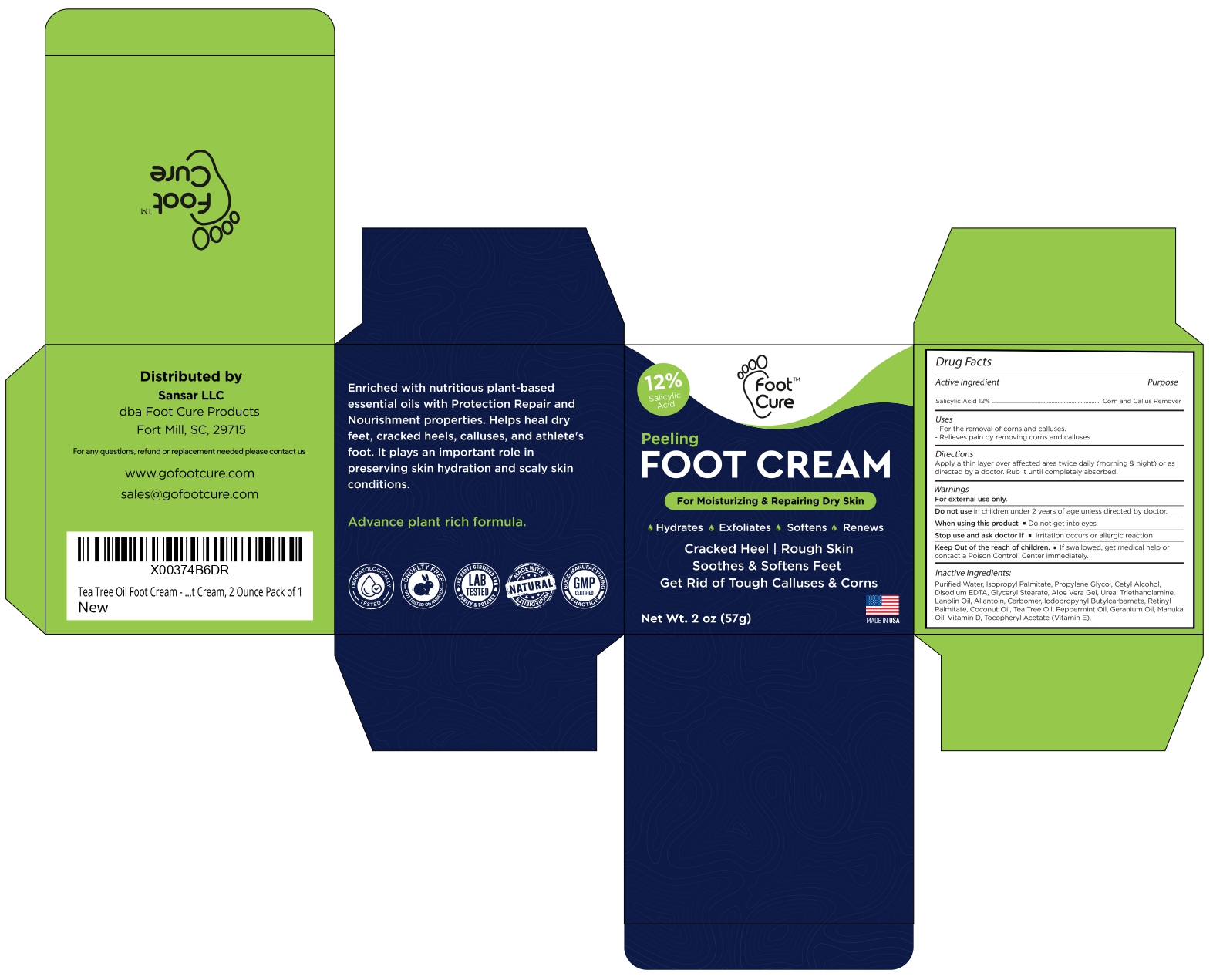 DRUG LABEL: Salicylic Acid
NDC: 83691-008 | Form: CREAM
Manufacturer: SANSAR, LLC
Category: otc | Type: HUMAN OTC DRUG LABEL
Date: 20250616

ACTIVE INGREDIENTS: SALICYLIC ACID 12 g/100 g
INACTIVE INGREDIENTS: ISOPROPYL PALMITATE; PROPYLENE GLYCOL; CETYL ALCOHOL; EDETATE DISODIUM; GLYCERYL MONOSTEARATE; ALOE VERA LEAF; UREA; TROLAMINE; LANOLIN OIL; ALLANTOIN; CARBOMER HOMOPOLYMER, UNSPECIFIED TYPE; IODOPROPYNYL BUTYLCARBAMATE; VITAMIN A PALMITATE; COCONUT OIL; TEA TREE OIL; PEPPERMINT OIL; PALMAROSA OIL; MANUKA OIL; VITAMIN D; .ALPHA.-TOCOPHEROL ACETATE

Salicylic Acid Foot Cream

Active ingredient

Salicylic acid 12%

Purpose

Corn and callus remover

Uses

- for the removal of corns and calluses
- Relieves pain by removing corns and calluses

Warnings

For external use only.

Do not use in Children under 2 years of age unless directed by doctor.

When using this product

- Do not get into eyes

Stop use and ask doctor if

- irritation occurs or allergic reaction

KEEP OUT OF REACH OF CHILDREN

Keep out of the reach of children. If swallowed, get medical help or contact a Poison Control Center immediately.

Directions

Apply a thin layer over affected area twice daily (morning & night) or as directed by a doctor. Rub it until completely absorbed.

Inactive Ingredients

Purified water, Isopropyl Palmitate, Propylene Glycol, Cetyl Alcohol, Disodium EDTA, Glyceryl Stearate, Aloe Vera Gel, Urea, Triethanolamine, Lanolin oil, Allantoin, Carbomer, Iodopropynyl Butylcarbamate, Retinyl Palmitate, Coconut Oil, Tea Tree Oil, Peppermint Oil, Geranium Oil, Manuka Oil, Vitamin D, Tocopheryl Acetate (Vitamin E).